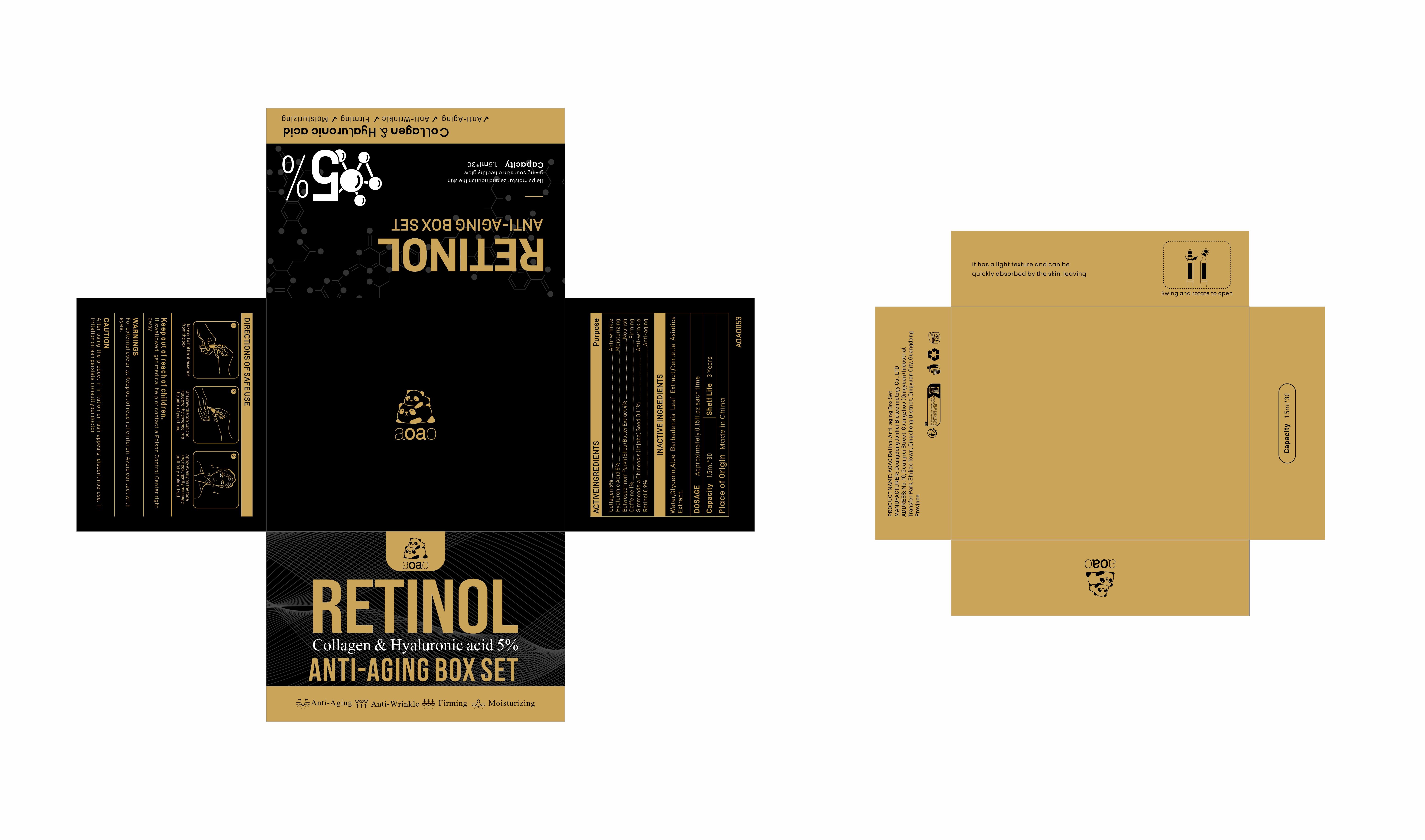 DRUG LABEL: AOAO Retinol Anti-aging Box Set
NDC: 84509-032 | Form: LIQUID
Manufacturer: Guangdong Junhui Biotechnology Co., LTD
Category: otc | Type: HUMAN OTC DRUG LABEL
Date: 20250108

ACTIVE INGREDIENTS: HYALURONIC ACID 2250 mg/45 mL; SHEA BUTTER 1800 mg/45 mL; COLLAGEN, SOLUBLE, FISH SKIN 2250 mg/45 mL; RETINOL 405 mg/45 mL; CAFFEINE 450 mg/45 mL; SIMMONDSIA CHINENSIS (JOJOBA) SEED OIL 450 mg/45 mL
INACTIVE INGREDIENTS: ALOE VERA LEAF; CENTELLA ASIATICA TRITERPENOIDS; WATER; GLYCERIN

Active Ingredients

Collagen 5%
Butyrospermum Parkii (Shea) Butter Extract 4%
Hyaluronic Acid 5%
Caffeine 1%
Simmondsia Chinensis (Jojoba) Seed Oil 1%
Retinol 0.9%

Purpose

Anti-wrinkle
Nourish
Moisturizing
Firming
Anti-aging

Inactive Ingredients

Water,Glycerin,Aloe Barbadensis Leaf Extract，Centella Asiatica Extract.

Warnings

For external use only. Keep out ofreach of children.Avoid contact with eyes

Keep out of reach of children

If swallowed, get medical help or contact a Poison Control Center right away

CAUTION

After using the product if irritation or rash appears,discontinue use.If irritation or
rash persists.consult your doctor.

DOSAGE

Approximately 0.15fl.oz each time

Uses

1. Take out a bottle of essence from the box
2. Unscrew the top cap and squeeze the essence into the palm of your hand
3. Apply evenly on the face and neck, gently massage until fully moisturized

Product Name

AOAO Retinol Anti-aging Box Set

Manufacturer

Guangdong Junhui Biotechnology Co., LTD

ADDRESS

No. 10, Guangrui Street, Guangzhou (Qingyuan) Industrial Transfer Park, Shijiao Town, Qingcheng District, Qingyuan City, Guangdong Province

Capacity

1.5ml*30

Shelf Life

3 Years

Place of Origin

Made in China